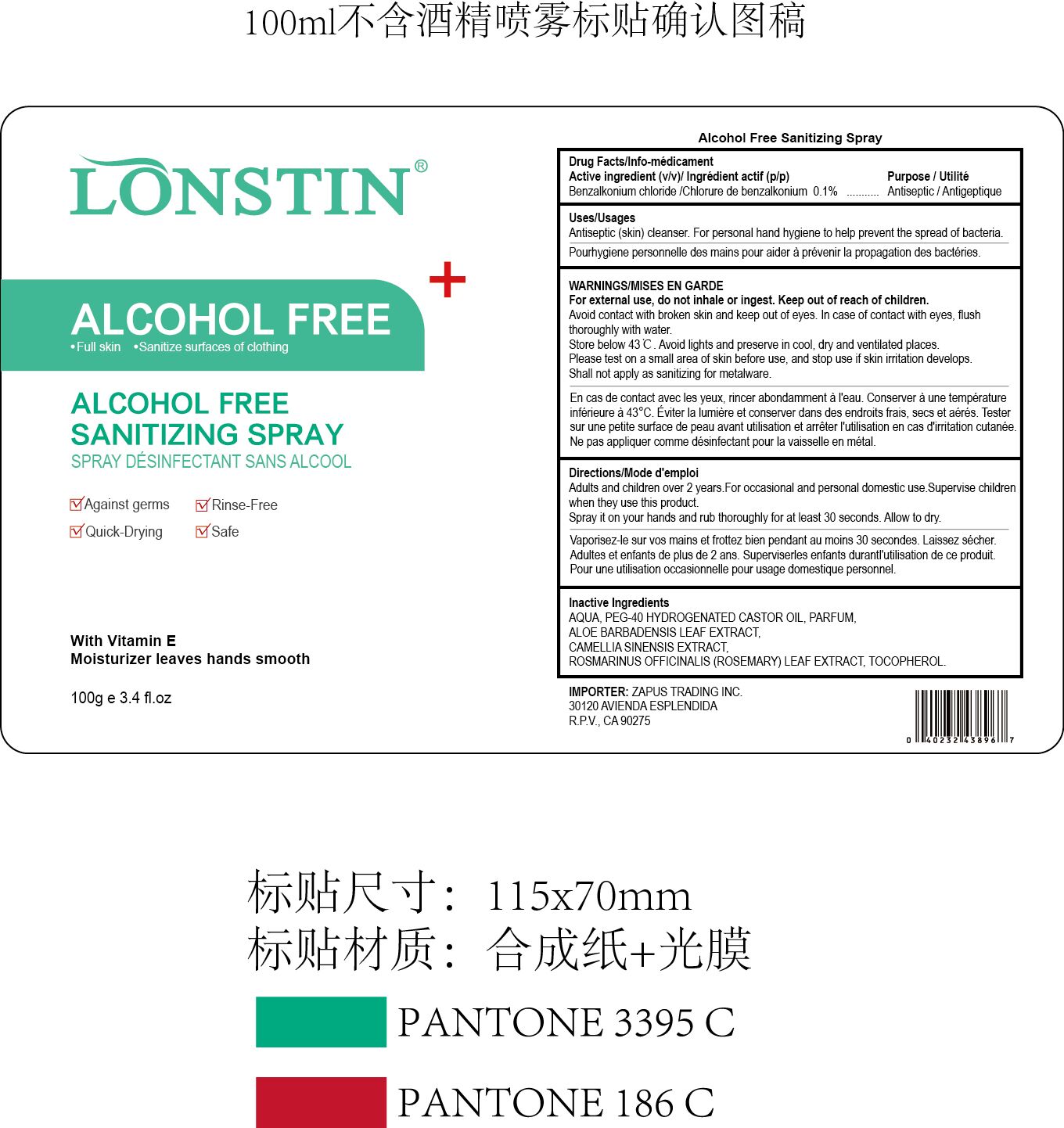 DRUG LABEL: ALCOHOL FREE SANITIZING
NDC: 74743-003 | Form: SPRAY
Manufacturer: Guangzhou Joy Claire Biological Technology Co., Ltd
Category: otc | Type: HUMAN OTC DRUG LABEL
Date: 20200726

ACTIVE INGREDIENTS: BENZALKONIUM CHLORIDE 0.1 g/100 g
INACTIVE INGREDIENTS: WATER; POLYOXYL 40 HYDROGENATED CASTOR OIL; METHYL BENZOATE; ALOE VERA LEAF; CAMELLIA SINENSIS WHOLE; ROSEMARY; TOCOPHEROL

ALCOHOL FREE SANITIZING SPRAY

Active Ingredients

Benzalkonium chloride 0.1%

Purpose

Antiseptic

Uses

Antiseptic (skin) cleanser.For personal hand hygiene to help

prevent the spread of bacteria.

WARNINGS

For external use, do not inhale or ingest. Keep out of reach of children.
Avoid contact with broken skin and keep out of eyes. In case of contact with eyes, flush thoroughly with water.
Store below 43℃. Avoid lights and preserve in cool, dry and ventilated places.
Please test on a small area of skin before use, and stop use if skin irritation develops.
Shall not apply as sanitizing for metalware.

DO NOT USE

/

WHEN USING

/

STOP USE

/

Keep out of reach of children.
Avoid contact with broken skin and keep out of eyes. In case of contact with eyes, flush thoroughly with water.

Directions

Adults and children over 2 years.For occasional and personal domestic use.Supervise children when they use this product.
Spray it on your hands and rub thoroughly for at least 30 seconds. Allow to dry.

STORAGE AND HANDLING

Store below 43℃. Avoid lights and preserve in cool, dry and ventilated places.
Please test on a small area of skin before use, and stop use if skin irritation develops.
Shall not apply as sanitizing for metalware.

INACTIVE INGREDIENT

AQUA, PEG-40 HYDROGENATED CASTOR OIL,PARFUM, ALOE BARBADENSIS LEAF EXTRACT, CAMELLIA SINENSIS EXTRACT, ROSMARINUS OFFICINALIS (ROSEMARY) LEAF EXTRACT, TOCOPHEROL.